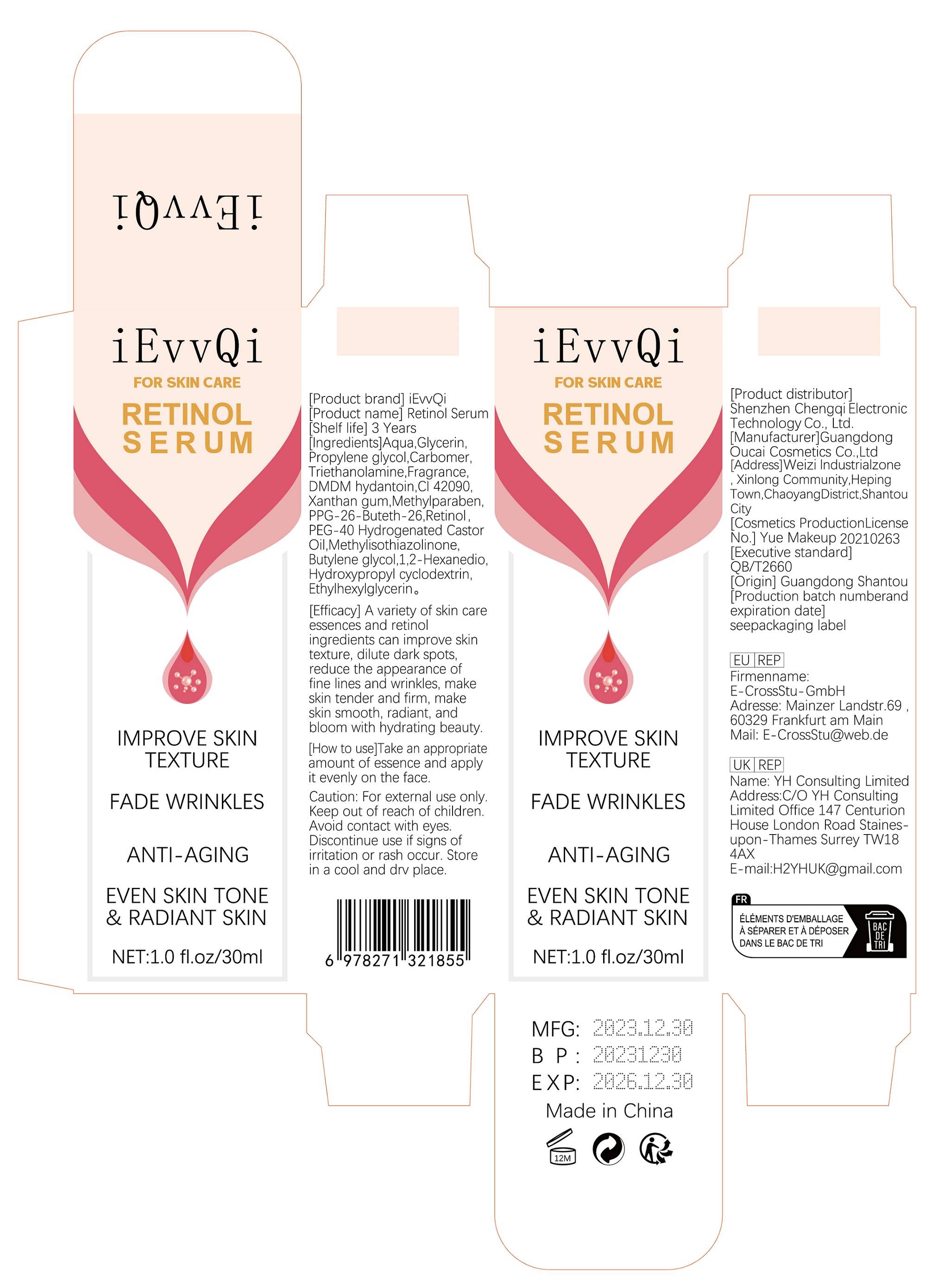 DRUG LABEL: Retinol Serum
NDC: 84118-003 | Form: LIQUID
Manufacturer: Shenzhen Chengqi Electronic Science & Technology Co., Ltd.
Category: otc | Type: HUMAN OTC DRUG LABEL
Date: 20240313

ACTIVE INGREDIENTS: GLYCERIN 10 g/100 mL
INACTIVE INGREDIENTS: WATER

active ingredients

GLYCERIN 10%

inactive ingredients

Aqua

Propylene Glycol
Carbomer
Triethanolamine
DMDM Hydantoin
Xanthan Gum
Methylparaben
PPG-26-Buteth-26
PEG-40 Hydrogenated Castor Oil
Fragrance
CI 42090
Butylene Glycol
Methylisothiazolinone
Hydroxypropyl Cyclodextrin
Retinol
1,2-Hexanediol
Ethylhexylglycerin

Purpose

Moisturizing

WARNINGS

For external use only

Stop use and ask a doctor if

rash occurs

DO NOT USE

on damaged or broken skin

When using this product

keep out of eyes. Rinse with water to remove

Keep out of reach of children.

If swallwed, get medical help or contact a Poison Control Center right away

Uses

Keep skin moisturized

DOSAGE & ADMINISTRATION

Take an appropriate amount of this product and apply it to the skin